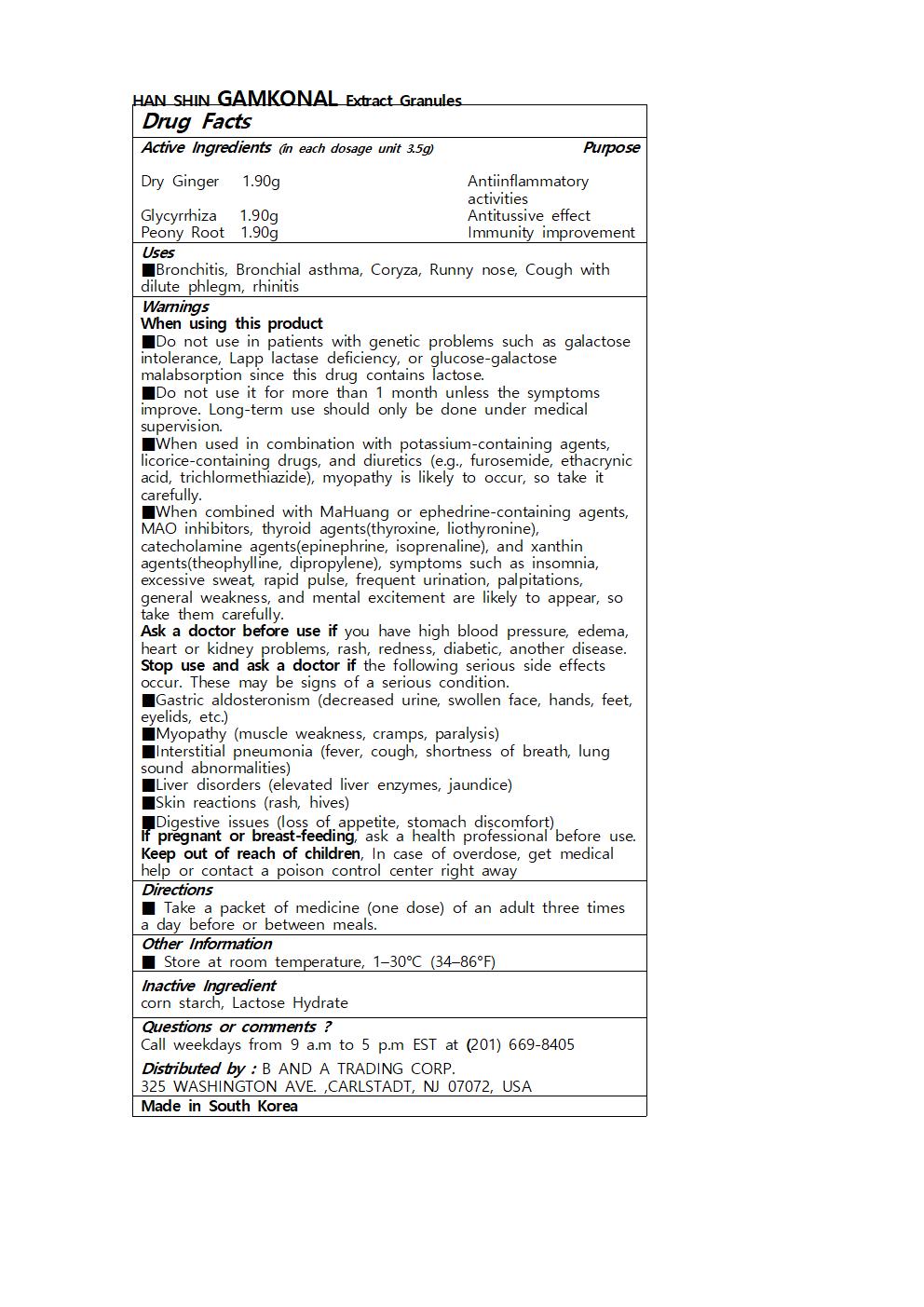 DRUG LABEL: HAN SHIN GAMKONAL Extract Granules
NDC: 73466-0033 | Form: GRANULE
Manufacturer: MISOCOS
Category: otc | Type: HUMAN OTC DRUG LABEL
Date: 20250301

ACTIVE INGREDIENTS: PAEONIA LACTIFLORA ROOT 1.9 g/3.5 g; GINGER 1.9 g/3.5 g; LICORICE 1.9 g/3.5 g
INACTIVE INGREDIENTS: LACTOSE MONOHYDRATE

Drug Facts

ACTIVE INGREDIENT

Dry Ginger 1.90g

Glycyrrhiza 1.90g

Peony Root 1.90g

INACTIVE INGREDIENT

corn starch, Lactose Hydrate

PURPOSE

■Bronchitis, Bronchial asthma, Coryza, Runny nose, Cough with dilute phlegm, rhinitis

keep out of reach of the children

INDICATIONS AND USAGE

■ Take a packet of medicine (one dose) of an adult three times a day before or between meals.

Warnings

When using this product

■Do not use in patients with genetic problems such as galactose intolerance, Lapp lactase deficiency, or glucose-galactose malabsorption since this drug contains lactose.

■Do not use it for more than 1 month unless the symptoms improve. Long-term use should only be done under medical supervision.

■When used in combination with potassium-containing agents, licorice-containing drugs, and diuretics (e.g., furosemide, ethacrynic acid, trichlormethiazide), myopathy is likely to occur, so take it carefully.

■When combined with MaHuang or ephedrine-containing agents, MAO inhibitors, thyroid agents(thyroxine, liothyronine), catecholamine agents(epinephrine, isoprenaline), and xanthin agents(theophylline, dipropylene), symptoms such as insomnia, excessive sweat, rapid pulse, frequent urination, palpitations, general weakness, and mental excitement are likely to appear, so take them carefully.

Ask a doctor before use if you have high blood pressure, edema, heart or kidney problems, rash, redness, diabetic, another disease.

Stop use and ask a doctor if the following serious side effects occur. These may be signs of a serious condition.

■Gastric aldosteronism (decreased urine, swollen face, hands, feet, eyelids, etc.)

■Myopathy (muscle weakness, cramps, paralysis)

■Interstitial pneumonia (fever, cough, shortness of breath, lung sound abnormalities)

■Liver disorders (elevated liver enzymes, jaundice)

■Skin reactions (rash, hives)

■Digestive issues (loss of appetite, stomach discomfort)

If pregnant or breast-feeding, ask a health professional before use.

Keep out of reach of children, In case of overdose, get medical help or contact a poison control center right away

DOSAGE AND ADMINISTRATION

for oral use only